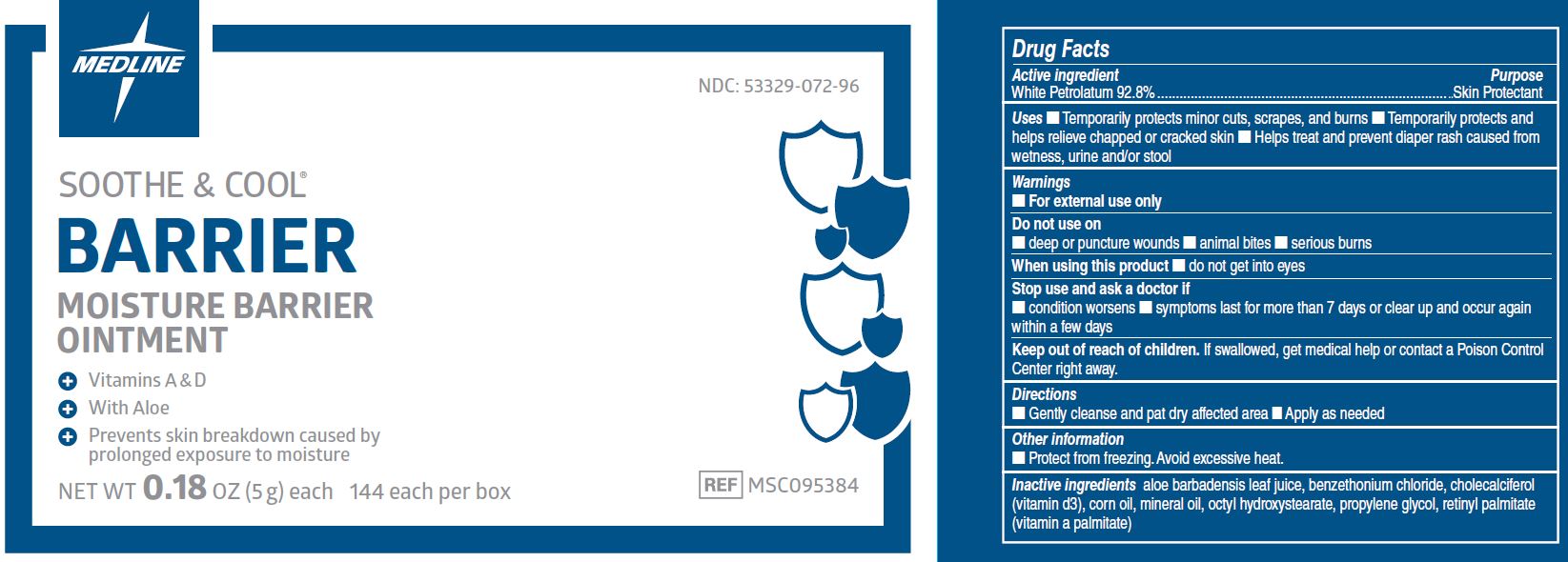 DRUG LABEL: Soothe and Cool Free Moisture Barrier
NDC: 53329-072 | Form: OINTMENT
Manufacturer: Medline Industries, LP
Category: otc | Type: HUMAN OTC DRUG LABEL
Date: 20220927

ACTIVE INGREDIENTS: PETROLATUM 92.8 g/100 g
INACTIVE INGREDIENTS: ALOE VERA LEAF; BENZETHONIUM CHLORIDE; CHOLECALCIFEROL; ISOPROPYL MYRISTATE; PROPYLENE GLYCOL; VITAMIN A PALMITATE

072 Soothe and Cool® Moisture Barrier

Active ingredient

Petrolatum 92.8%

Purpose

Skin Protectant

Uses

- Temporarily protects minor cuts, scrapes, and burns
- temporarily protects and helps chapped or cracked skin and lips
- helps treat and prevent diaper rash caused from wetness, urine and/or stool

Warnings

For external use only.

Do not use on

- deep or puncture wounds
- animal bites
- serious burns

When using this product

- do not get into eyes

Stop use and ask a doctor if

- Condition worsens
- Symptoms last for more than 7 days or clear up and occur again within a few days

Keep out of reach of children.

If swallowed, get medical help or consult a Poison Control Center right away.

Directions

- gently cleanse and pat dry affected area
- apply ointment as needed

Other information

- protect from freezing, avoid excessive heat

Inactive ingredients

aloe barbadensis leaf juice, benzethonium chloride, cholecalciferol (vitamin D3), corn oil, mineral oil, octyl hydroxystearate, propylene glycol, retinyl palmitate (vitamin A)

Manufacturing Information

Manufactured for: Medline Industries, Inc.

Three Lakes Drive, Northfield, IL 60093 USA

Made in USA

www.medline.com

1-800-MEDLINE

REF: MSC095384

RK19ULI